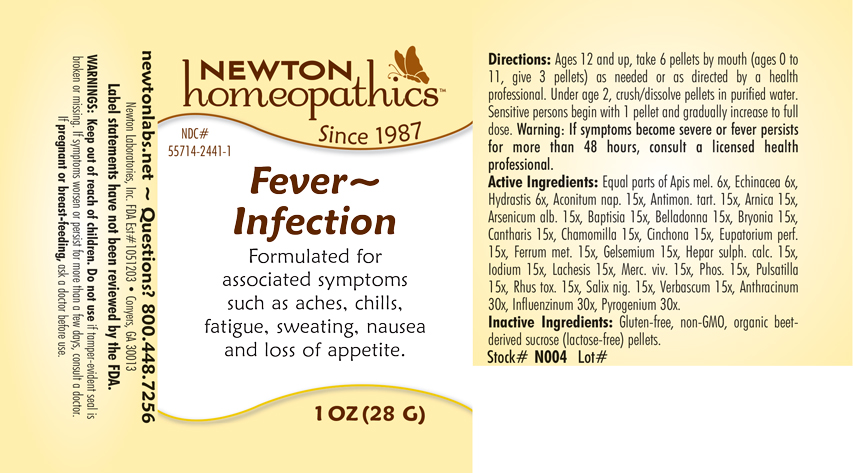 DRUG LABEL: Fever - Infection
NDC: 55714-2441 | Form: PELLET
Manufacturer: Newton Laboratories, Inc.
Category: homeopathic | Type: HUMAN OTC DRUG LABEL
Date: 20250206

ACTIVE INGREDIENTS: BACILLUS ANTHRACIS IMMUNOSERUM RABBIT 30 [hp_X]/1 g; INFLUENZA A VIRUS 30 [hp_X]/1 g; RANCID BEEF 30 [hp_X]/1 g; ACONITUM NAPELLUS 15 [hp_X]/1 g; BAPTISIA TINCTORIA 15 [hp_X]/1 g; ANTIMONY POTASSIUM TARTRATE 15 [hp_X]/1 g; ARNICA MONTANA 15 [hp_X]/1 g; ARSENIC TRIOXIDE 15 [hp_X]/1 g; ATROPA BELLADONNA 15 [hp_X]/1 g; BRYONIA ALBA ROOT 15 [hp_X]/1 g; LYTTA VESICATORIA 15 [hp_X]/1 g; MATRICARIA RECUTITA 15 [hp_X]/1 g; CINCHONA OFFICINALIS BARK 15 [hp_X]/1 g; EUPATORIUM PERFOLIATUM FLOWERING TOP 15 [hp_X]/1 g; IRON 15 [hp_X]/1 g; GELSEMIUM SEMPERVIRENS ROOT 15 [hp_X]/1 g; CALCIUM SULFIDE 15 [hp_X]/1 g; IODINE 15 [hp_X]/1 g; LACHESIS MUTA VENOM 15 [hp_X]/1 g; MERCURY 15 [hp_X]/1 g; PHOSPHORUS 15 [hp_X]/1 g; PULSATILLA VULGARIS 15 [hp_X]/1 g; TOXICODENDRON PUBESCENS LEAF 15 [hp_X]/1 g; SALIX NIGRA BARK 15 [hp_X]/1 g; VERBASCUM THAPSUS 15 [hp_X]/1 g; APIS MELLIFERA 6 [hp_X]/1 g; ECHINACEA, UNSPECIFIED 6 [hp_X]/1 g; GOLDENSEAL 6 [hp_X]/1 g; INFLUENZA B VIRUS 30 [hp_X]/1 g
INACTIVE INGREDIENTS: SUCROSE

Fever 2441P

INDICATIONS & USAGE SECTION

Formulated for associated symptoms such as aches, chills, fatigue, sweating, nausea and loss of appetite.

DOSAGE & ADMINISTRATION SECTION

Directions: Ages 12 and up, take 6 pellets mouth (ages 0 to 11, give 3 pellets) as needed or as directed by a health professional. Under age 2, crush or dissolve pellets in purfied water. Sensitive persons begin with 1 pellet and gradually increase to full dose. Warning: If symptoms become severe or fever persists for more than 48 hours, consult a licensed health professional.

OTC - ACTIVE INGREDIENT SECTION

Equal parts of Apis mel. 6x, Echinacea 6x, Hydrastis 6x, Aconitum nap. 15x, Antimon. tart. 15x, Arnica 15x, Arsenicum alb. 15x, Baptisia 15x, Belladonna 15x, Bryonia 15x, Cantharis 15x, Chamomilla 15x, Cinchona 15x, Eupatorium perf. 15x, Ferrum metallicum 15x, Gelsemium 15x, Hepar sulph.calc. 15x, Iodium 15x, Lachesis 15x, Merc. viv. 15x, Phosphorus 15x, Pulsatilla 15x, Rhus toxicodendron 15x, Salix nigra 15x, Verbascum 15x, Anthracinum 30x, Influenzinum 30x, Pyrogenium 30x.

OTC - PURPOSE SECTION

Formulated for associated symptoms such as aches, chills, fatigue, sweating, nausea and loss of appetite

INACTIVE INGREDIENT SECTION

Inactive Ingredients: Gluten-Free, non-GMO, organic beet-derived sucrose (lactose-free) pellets.

QUESTIONS SECTION

newtonlabs.net - Question? 800.448.7256

Newton Laboratories, Inc. FDA Est # 1051203 - Conyers, GA 30013

WARNINGS SECTION

WARNINGS: Keep out of reach of children. Do no use if tamper-evident seal is broken or missing. If pregnant or breast-feeding, ask a doctor before use.

OTC - PREGNANCY OR BREAST FEEDING SECTION

If pregnant or breast-feeding, ask a doctor before use.

OTC - KEEP OUT OF REACH OF CHILDREN SECTION

Keep out of reach of children.